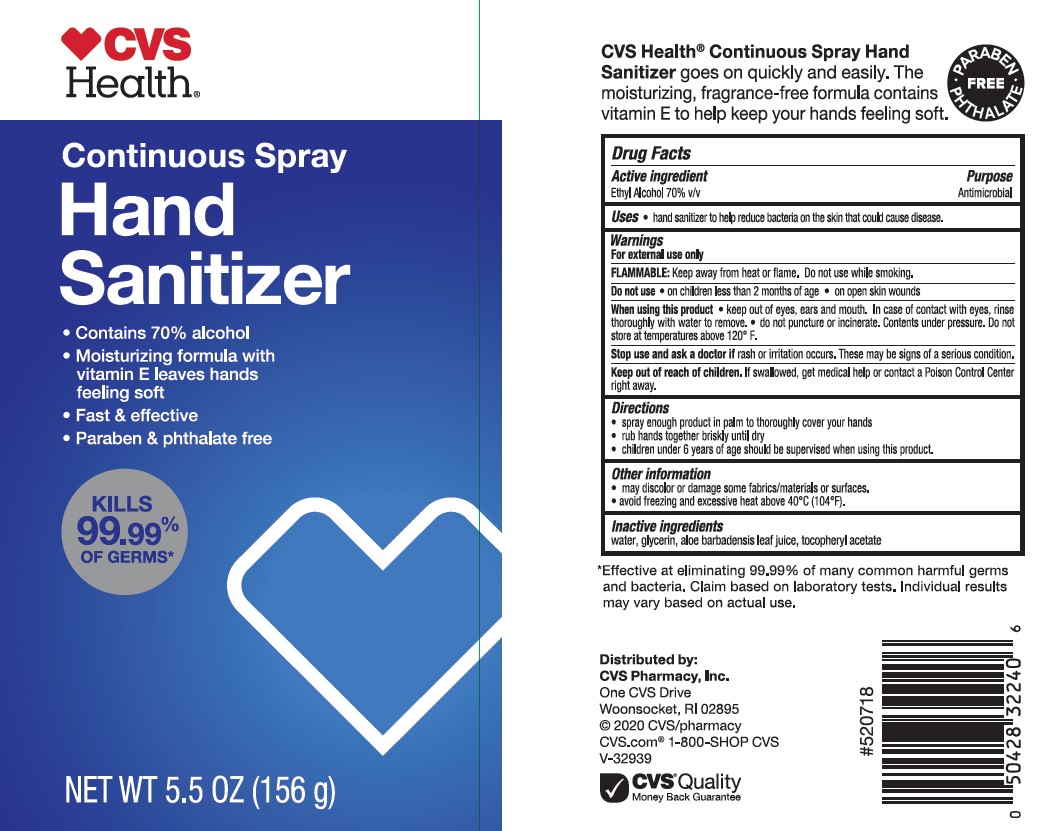 DRUG LABEL: CVS HEALTH CONTINUOUS HAND SANITIZER
NDC: 69842-455 | Form: AEROSOL, SPRAY
Manufacturer: CVS PHARMACY
Category: otc | Type: HUMAN OTC DRUG LABEL
Date: 20241022

ACTIVE INGREDIENTS: ALCOHOL 70 mg/100 g
INACTIVE INGREDIENTS: GLYCERIN; ALOE VERA LEAF; WATER; .ALPHA.-TOCOPHEROL ACETATE

CVS HEALTH CONTINUOUS SPRAY HAND SANITIZER

Active Ingredients

Ethyl Alcohol 70% v/v

Purpose

Antimicrobial

Uses

- hand sanitizer to help reduce bacteria on the skin that could cause disease.

Warnings

For external use only.

Flammable.

Keep away from heat or flame

Do not use

- in children less than 2 months of age
- on open skin wounds

When using this product

- keep out of eyes, ears, and mouth. In case of contact with eyes, rinse eyes thoroughly with water to remove.
- do not puncture or incinerate. Contents under pressure. Do not store at temperatures above 120ºF.

Stop use and ask a doctor if

rash or irritation occurs. These may be signs of a serious condition.

Keep out of reach of children.

If swallowed, get medical help or contact a Poison Control Center right away.

Directions

- spray enough product in palm to thoroughly cover your hands
- rub hands together briskly until dry
- children under 6 years of age should be supervised when using this product.

Other information

- may discolor or damage some fabrics/materials or surfaces.
- Avoid freezing and excessive heat above 40ºC (104ºF)

Inactive ingredients

water, glycerin, aloe barbadensis leaf juice, tocopheryl acetate